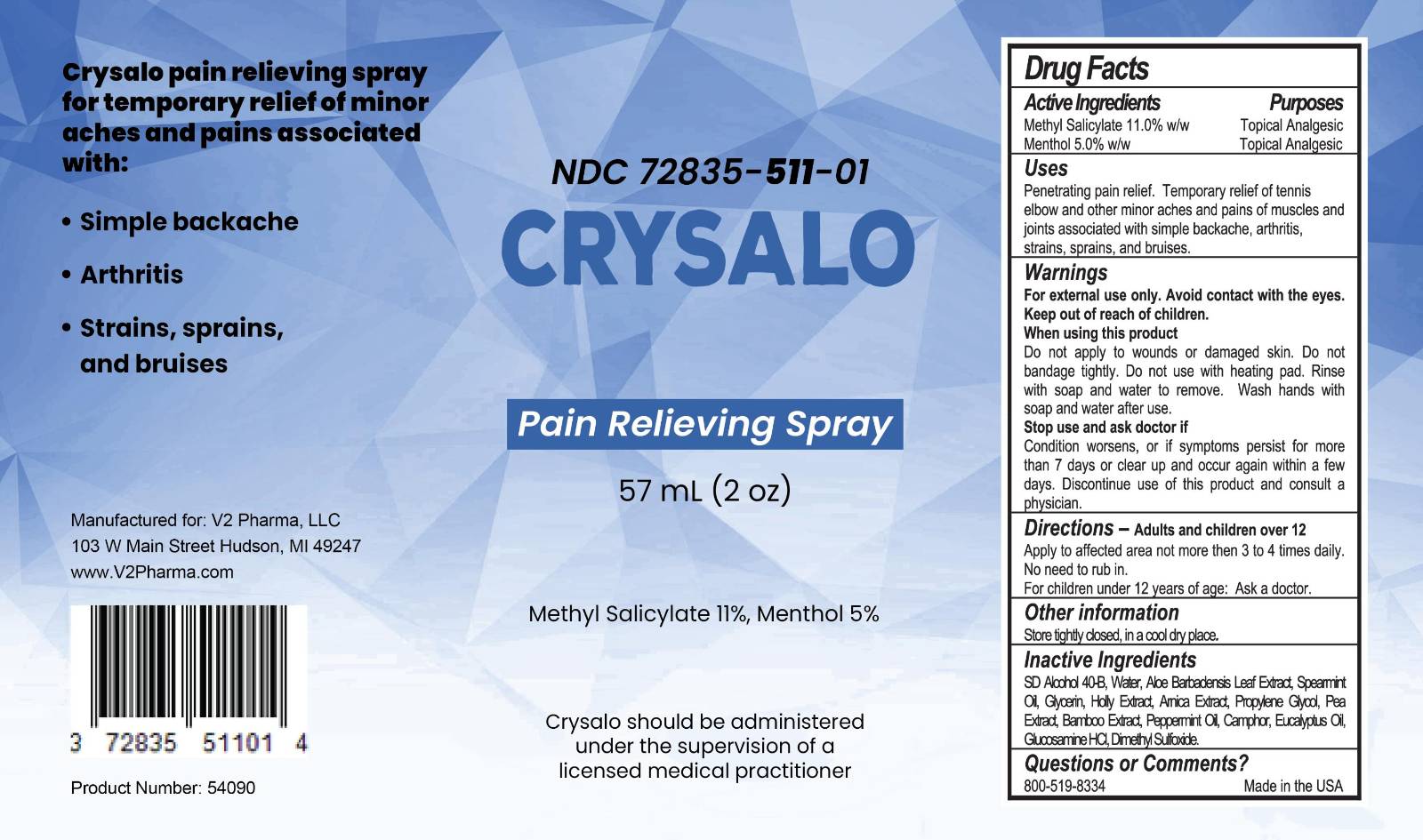 DRUG LABEL: Crysalo
NDC: 72835-511 | Form: LIQUID
Manufacturer: V2 Pharma, LLC
Category: otc | Type: HUMAN OTC DRUG LABEL
Date: 20250828

ACTIVE INGREDIENTS: METHYL SALICYLATE 11 g/100 mL; MENTHOL 5 g/100 mL
INACTIVE INGREDIENTS: ALCOHOL; ALOE VERA LEAF JUICE; PRUNUS ILICIFOLIA WHOLE; water; ARNICA MONTANA FLOWER; BAMBUSA VULGARIS TOP; CAMPHOR (SYNTHETIC); EUCALYPTUS ROBUSTA LEAF OIL; PEPPERMINT OIL; DIMETHYL SULFOXIDE; SPEARMINT OIL; GLUCOSAMINE HCL; PEA; GLYCERIN; PROPYLENE GLYCOL

Crysalo

Crysalo

Pain Relieving Spray

Crysalo should be administered under the supervision of a licensed medical practitioner.

Uses

Temporary relief of minor aches and pains associated with:

- Simple backache
- Arthritis
- Strains, sprains, and bruises

Directions Adults and children 12 years of age and older:

Apply to affected area not more then 3 to 4 times daily.
No need to rub in.
For children under 12 years of age: Ask a doctor.

Fore external use only. Avoid contact with the eyes. Keep out of reach of children.

When using this product
Do not apply to wounds or damaged skin. Do not bandage tightly. Do not use with heating pad. Rinse with soap and water to remove. Wash hands with soap and water after use.

Stop use and ask doctor if:

Condition worsens, or if symptoms persist for more than 7 days or clear up and occur again within a few days. Discontinue use of this product and consult a physician.

Instructions for using Crysalo:

- Remove cap to expose spray applicator.
- Avoid contact with the eyes, lips, nose, genetalia and other mucous membranes.
- Hold spray bottle close (2-3 inches) to affected area and apply liberally 3 to 4 times daily.
- Do not use hands to rub in.
- Place cap back on and Wash hands thoroughly with soap and water.
- Allow treated area to dry naturally for best results.

STORAGE AND HANDLING

Store tightly closed in a cool dry place.

INACTIVE INGREDIENT

SD Alcohol 40-B, Water, Aloe Barbadensis Leaf Extract, Spearmint Oil, Glycerin, Holly Extract, Arnica Extract, Propylene Glycol, Pea Extract, Bamboo Extract, Peppermint Oil, Camphor, Eucalyptus Oil, Glucosamine HCl, Dimethyl Sulfoxide.

Manufactured for:
V2 Pharma, LLC
103 W Main Street
Hudson, MI 49247

Questions or concerns call 1-(800)-519-8334